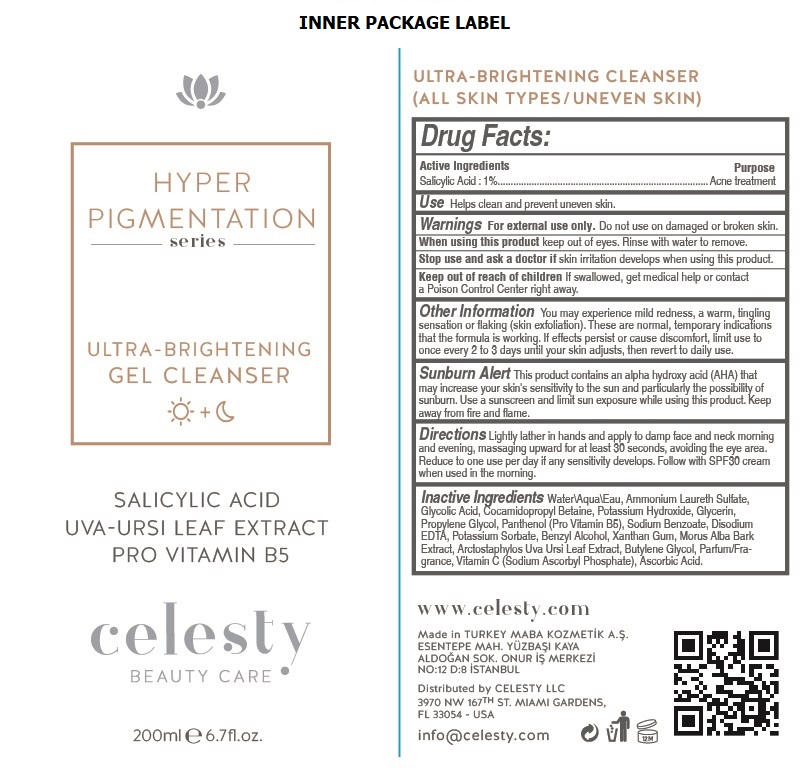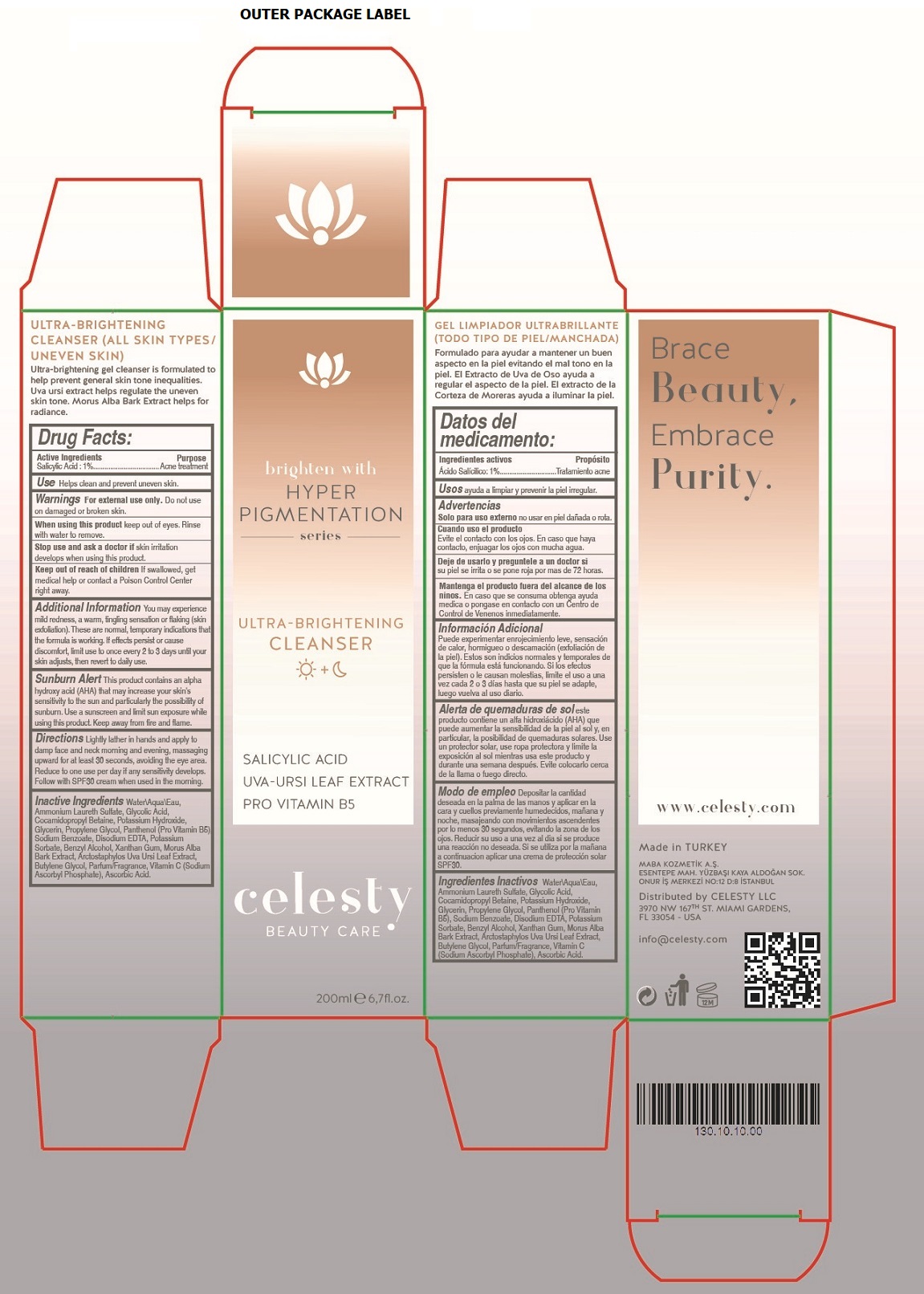 DRUG LABEL: Celesty
NDC: 81120-112 | Form: GEL
Manufacturer: MABA KOZMETIK LIMITED SIRKETI
Category: otc | Type: HUMAN OTC DRUG LABEL
Date: 20201210

ACTIVE INGREDIENTS: SALICYLIC ACID 1 g/100 mL
INACTIVE INGREDIENTS: WATER; AMMONIUM LAURETH-2 SULFATE; GLYCOLIC ACID; COCAMIDOPROPYL BETAINE; POTASSIUM HYDROXIDE; GLYCERIN; PROPYLENE GLYCOL; DEXPANTHENOL; SODIUM BENZOATE; EDETATE DISODIUM ANHYDROUS; POTASSIUM SORBATE; BENZYL ALCOHOL; XANTHAN GUM; MORUS ALBA BARK; ARCTOSTAPHYLOS UVA-URSI LEAF; BUTYLENE GLYCOL; SODIUM ASCORBYL PHOSPHATE; ASCORBIC ACID

celesty HYPERPIGMENTATION series ULTRA-BRIGHTENING GEL CLEANSER

Active Ingredients

Salicylic Acid : 1%

Purpose

Acne treatment

Use

Helps clean and prevent uneven skin.

Warnings

For external use only. Do not use on damaged or broken skin.

When using this product keep out of eyes. Rinse with water to remove.

Stop use and ask a doctor if skin irritation develops when using this product.

Keep out of reach of children If swallowed, get medical help or contact a Poison Control Center right away.

Additional Information

You may experience mild redness, a warm, tingling sensation or flaking (skin exfoliation). These are normal, temporary indications that the formula is working. If effects persist or cause discomfort, limit use to once every 2 to 3 days until skin adjusts, then revert to daily use.

Sunburn Alert This product contains an alpha hydroxy acid (AHA) that may increase your skin's sensitivity to the sun and particularly the possibility of sunburn. Use a sunscreen and limit sun exposure while using this product. Keep away from fire and flame.

Directions

Lightly lather in hands and apply to damp face and neck morning and evening, massaging upward for at least 30 seconds, avoiding the eye area. Reduce to one use per day if any sensitivity develops. Follow with SPF30 cream when used in the morning.

Inactive Ingredients

Water\Aqua\Eau, Ammonium Laureth Sulfate, Glycolic Acid, Cocamidopropyl Betaine, Potassium Hydroxide, Glycerin, Propylene Glycol, Panthenol (Pro Vitamin B5), Sodium Benzoate, Disodium EDTA, Potassium Sorbate, Benzyl Alcohol, Xanthan Gum, Morus Alba Bark Extract, Arctostaphylos Uva Ursi Leaf Extract, Butylene Glycol, Parfum/Fragrance, Vitamin C (Sodium Ascorbyl Phosphate), Ascorbic Acid.

brighten with HYPERPIGMENTATION series

SALICYLIC ACID

UVA-URSI LEAF EXTRACT

PRO VITAMIN B5

BEAUTY CARE

(ALL SKIN TYPES / UNEVEN SKIN)

Ultra-brightening gel cleanser is formulate to help prevent general skin tone inequalities.

Uva ursi extract helps regulate the uneven skin tone. Morus Alba Bark Extract helps for radiance.

Brace Beauty, Embrace Purity.

www.celesty.com

Made in TURKEY

MABA KOZMETIK A.S.

ESENTEPE MAH. YUZBASI KAYA ALDOGAN SOK.

ONUR IS MERKEZI NO:12 D:8 ISTANBUL

Distributed by CELESTY LLC

3970 NW 167TH ST. MIAMI GARDENS,

FL 33054 - USA

info@celesty.com